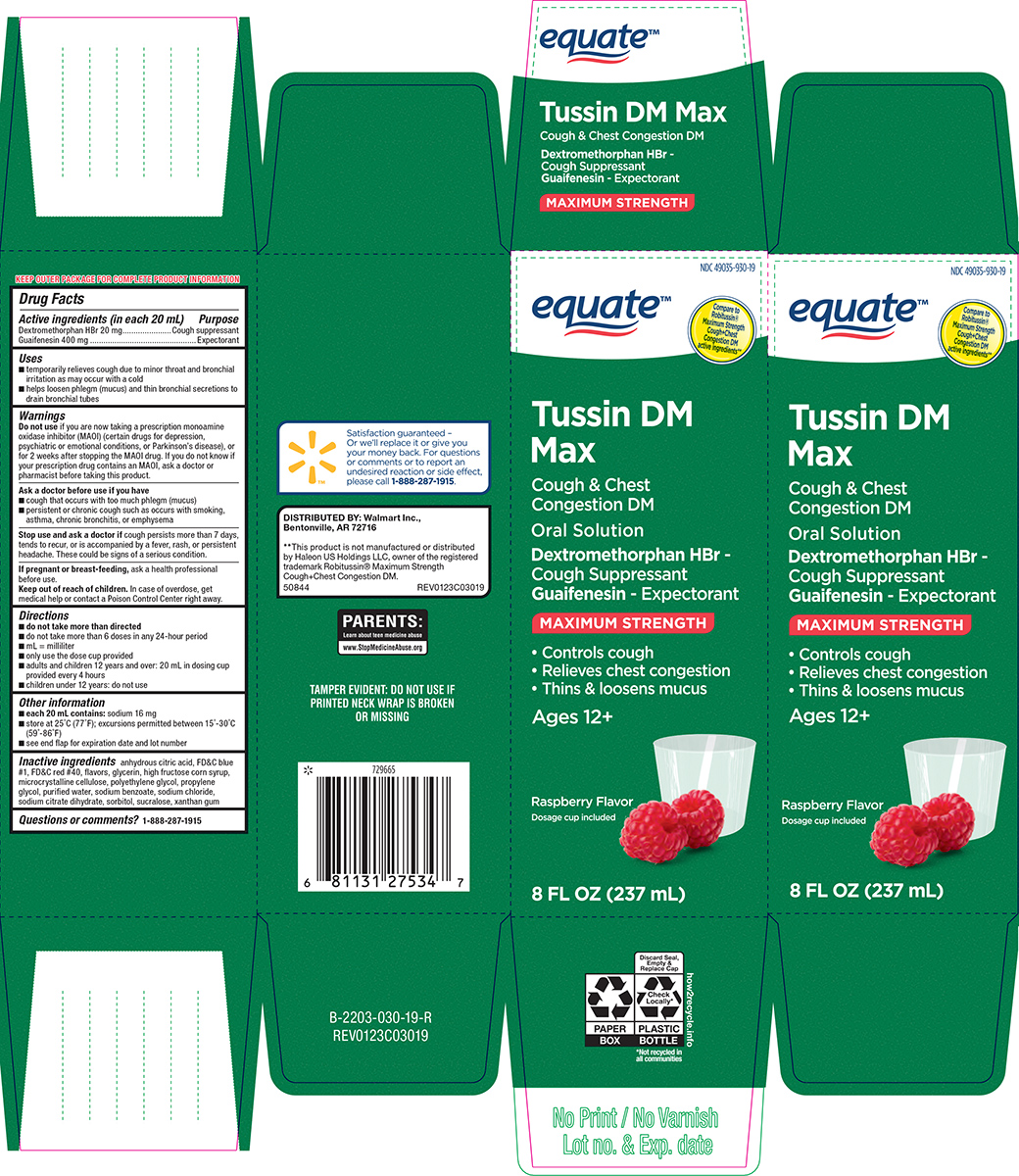 DRUG LABEL: Tussin DM Max
NDC: 49035-930 | Form: SOLUTION
Manufacturer: Wal-Mart Stores Inc
Category: otc | Type: HUMAN OTC DRUG LABEL
Date: 20260113

ACTIVE INGREDIENTS: DEXTROMETHORPHAN HYDROBROMIDE 20 mg/20 mL; GUAIFENESIN 400 mg/20 mL
INACTIVE INGREDIENTS: ANHYDROUS CITRIC ACID; FD&C BLUE NO. 1; FD&C RED NO. 40; GLYCERIN; HIGH FRUCTOSE CORN SYRUP; MICROCRYSTALLINE CELLULOSE; POLYETHYLENE GLYCOL, UNSPECIFIED; PROPYLENE GLYCOL; WATER; SODIUM BENZOATE; SODIUM CHLORIDE; TRISODIUM CITRATE DIHYDRATE; SORBITOL; SUCRALOSE; XANTHAN GUM

Equate 44-030

Active ingredients (in each 20 mL)

Dextromethorphan HBr 20 mg
Guaifenesin 400 mg

Purpose

Cough suppressant
Expectorant

Uses

- temporarily relieves cough due to minor throat and bronchial irritation as may occur with a cold
- helps loosen phlegm (mucus) and thin bronchial secretions to drain bronchial tubes

Warnings

Do not use

if you are now taking a prescription monoamine oxidase inhibitor (MAOI) (certain drugs for depression, psychiatric or emotional conditions, or Parkinson's disease), or for 2 weeks after stopping the MAOI drug. If you do not know if your prescription drug contains an MAOI, ask a doctor or pharmacist before taking this product.

Ask a doctor before use if you have

- cough that occurs with too much phlegm (mucus)
- persistent or chronic cough such as occurs with smoking, asthma, chronic bronchitis, or emphysema

Stop use and ask a doctor if

cough persists more than 7 days, tends to recur, or is accompanied by a fever, rash, or persistent headache. These could be signs of a serious condition.

If pregnant or breast-feeding,

ask a health professional before use.

Keep out of reach of children.

In case of overdose, get medical help or contact a Poison Control Center right away.

Directions

- do not take more than directed
- do not take more than 6 doses in any 24-hour period
- mL = milliliter
- only use the dose cup provided
- adults and children 12 years and over: 20 mL in dosing cup provided every 4 hours
- children under 12 years: do not use

Other information

- each 20 mL contains: sodium 16 mg
- store at 25°C (77°F); excursions permitted between 15°-30°C (59°-86°F)
- see end flap for expiration date and lot number

Inactive ingredients

anhydrous citric acid, FD&C blue #1, FD&C red #40, flavors, glycerin, high fructose corn syrup, microcrystalline cellulose, polyethylene glycol, propylene glycol, purified water, sodium benzoate, sodium chloride, sodium citrate dihydrate, sorbitol, sucralose, xanthan gum

Questions or comments?

1-888-287-1915

Principal Display Panel

NDC 49035-930-19

equate™

Compare to
Robitussin®
Maximum Strength
Cough+Chest
Congestion DM
active ingredients**

Tussin DM
Max

Cough & Chest
Congestion DM

Oral Solution

Dextromethorphan HBr -
Cough Suppressant
Guaifenesin - Expectorant

Maximum Strength

• Controls cough
• Relieves chest congestion
• Thins & loosens mucus

Ages 12+

Raspberry Flavor
Dosage cup included

8 FL OZ (237 mL)

TAMPER EVIDENT: DO NOT USE IF
PRINTED NECK WRAP IS BROKEN
OR MISSING

PARENTS:
Learn about teen medicine abuse
www.StopMedicineAbuse.org

Satisfaction guaranteed –
Or we’ll replace it or give you
your money back. For questions
or comments or to report an
undesired reaction or side effect,
please call 1-888-287-1915.

DISTRIBUTED BY: Walmart Inc.,
Bentonville, AR 72716

**This product is not manufactured or distributed
by Haleon US Holdings LLC, owner of the registered
trademark Robitussin® Maximum Strength
Cough+Chest Congestion DM.

50844 REV0123C03019

Equate 44-030